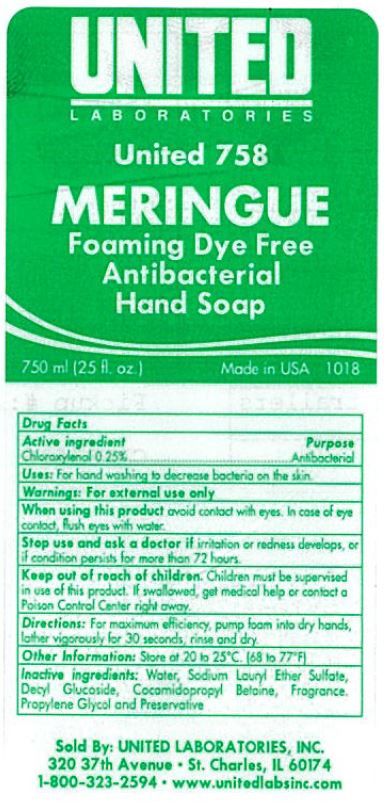 DRUG LABEL: Meringue Foaming Dye Free Antibacterial
NDC: 63998-758 | Form: LIQUID
Manufacturer: United Laboratories Inc.
Category: otc | Type: HUMAN OTC DRUG LABEL
Date: 20241125

ACTIVE INGREDIENTS: CHLOROXYLENOL 2.5 mg/1 mL
INACTIVE INGREDIENTS: WATER; COCAMIDOPROPYL BETAINE; DMDM HYDANTOIN; SODIUM LAURETH-3 SULFATE; DECYL GLUCOSIDE; PROPYLENE GLYCOL

63998-758

Active ingredient

Chloroxylenol 0.25%

Purpose

Antibacterial

Uses:

For hand washing to decrease bacteria on the skin.

Warnings:

For external use only

WHEN USING

When using this productavoid contact with eyes. In case of eye contact, flush eyes with water.

Stop use and ask a doctor ifirritation or redness develops, or if condition persists for more than 72 hours.

Keep out of reach of children.Children must be surpervised in use of this product. If swallowed, get medical help or contact a Poison Control center right away.

Directions:

For maximum efficiency, pump foam into dry hands, later vigorously for 30 seconds, rinse and dry.

Other Information:

Store at 20 to 25 C [68 to 77 F]

Inactive ingredients:

Water, Sodium Lauryl Ether Sulfate, Decyl Glucoside, Cocamidopropyl Betaine, Fragrance, Propylene Glycol and Preservative

PACKAGE LABEL

UNITED

Laboratories

United 758

MERINGUE

Foaming Dye Free

Antibacterial

Hand Soap

750 ml (25 fl.oz.) Made in USA 1018